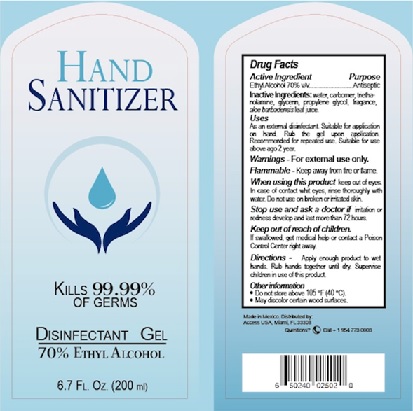 DRUG LABEL: Hand Sanitizer
NDC: 77106-002 | Form: GEL
Manufacturer: Resource Recovery & Trading LLC
Category: otc | Type: HUMAN OTC DRUG LABEL
Date: 20200512

ACTIVE INGREDIENTS: ALCOHOL 70 mL/100 mL
INACTIVE INGREDIENTS: WATER; CARBOMER HOMOPOLYMER, UNSPECIFIED TYPE; TROLAMINE; GLYCERIN; PROPYLENE GLYCOL; ALOE VERA LEAF

Active Ingredient

Ethyl Alcohol 70% v/v.

Purpose

Antiseptic

Uses

As an external disinfectant. Suitable for application on hand. Rub the gel upon application. Recommended for repeated use. Suitable fo use above ago 2 year.

Warnings

For external use only.

Flammable - Keep away from heat or flame.

When using this product avoid contact with the eyes. If contact occurs, rinse eyes thoroughly with water.
Stop using and ask doctor if irritation or redness develop and last more than 72 hours.

Keep out of reach of children. If swallowed, get medical help or contact a Poison Control Center right away.

Directions

Apply a small amount in your palm and rub hands together briskly until dry.

Children under 6 should be supervised when using this product.

Other information

Do not store above 105°F (40°C).

May discolor certain wood surfaces.

Questions ?
Call +1 954-773-0003

Inactive ingredients

Purified water, carbomer, triethanolamine, glycerin, propylene glycol, fragrance, Aloe Barbadensis leaf juice.